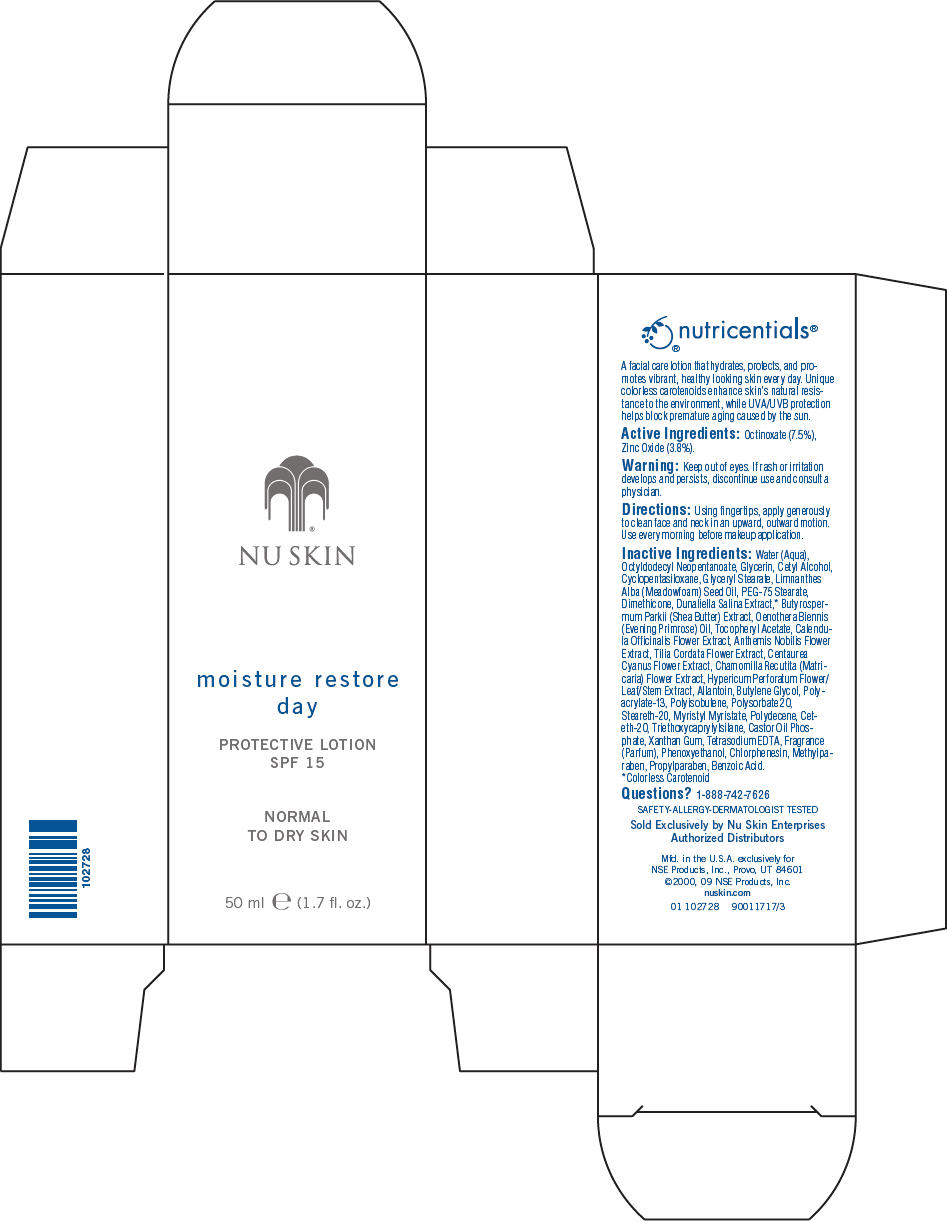 DRUG LABEL: Nu Skin
NDC: 62839-2728 | Form: LOTION
Manufacturer: NSE Products, Inc.
Category: otc | Type: HUMAN OTC DRUG LABEL
Date: 20220113

ACTIVE INGREDIENTS: Octinoxate 75 g/1000 mL; Titanium Dioxide 38 g/1000 mL
INACTIVE INGREDIENTS: Water; Octyldodecyl Neopentanoate; Glycerin; Cetyl Alcohol; Cyclomethicone 5; Glyceryl Monostearate; Meadowfoam Seed Oil; PEG-75 Stearate; Dimethicone; Sheanut Oil; Dunaliella Salina; Evening Primrose Oil; Calendula Officinalis Flower; Chamaemelum Nobile Flower; Tilia Cordata Flower; Centaurea Cyanus Flower; Chamomile; St. John's Wort; Allantoin; Butylene Glycol; Polysorbate 20; Steareth-20; Myristyl Myristate; Ceteth-20; Triethoxycaprylylsilane; Xanthan Gum; Edetate Sodium; Phenoxyethanol; Chlorphenesin; Methylparaben; Propylparaben; Benzoic Acid

NU SKIN
moisture restore
day
PROTECTIVE LOTION
SPF 15

Active Ingredients

Octinoxate (7.5%), Zinc Oxide (3.8%).

Warning

WHEN USING

Keep out of eyes. If rash or irritation develops and persists, discontinue use and consult a physician.

Directions

Using fingertips, apply generously to clean face and neck in an upward, outward motion. Use every morning before makeup application.

Inactive Ingredients

Water (Aqua), Octyldodecyl Neopentanoate, Glycerin, Cetyl Alcohol, Cyclopentasiloxane, Glyceryl Stearate, Limnanthes Alba (Meadowfoam) Seed Oil, PEG-75 Stearate, Dimethicone, Dunaliella Salina Extract, [Colorless Carotenoid] Butyrospermum Parkii (Shea Butter) Extract, Oenothera Biennis (Evening Primrose) Oil, Tocopheryl Acetate, Calendula Officinalis Flower Extract, Anthemis Nobilis Flower Extract, Tilia Cordata Flower Extract, Centaurea Cyanus Flower Extract, Chamomilla Recutita (Matricaria) Flower Extract, Hypericum Perforatum Flower/Leaf/Stem Extract, Allantoin, Butylene Glycol, Polyacrylate-13, Polyisobutene, Polysorbate 20, Steareth-20, Myristyl Myristate, Polydecene, Ceteth-20, Triethoxycaprylylsilane, Castor Oil Phosphate, Xanthan Gum, Tetrasodium EDTA, Fragrance (Parfum), Phenoxyethanol, Chlorphenesin, Methylparaben, Propylparaben, Benzoic Acid.

Questions?

1-888-742-7626

PRINCIPAL DISPLAY PANEL - 50 ml Carton

NU SKIN

moisture restore
day

PROTECTIVE LOTION
SPF 15

NORMAL
TO DRY SKIN

50 ml e (1.7 fl. oz.)